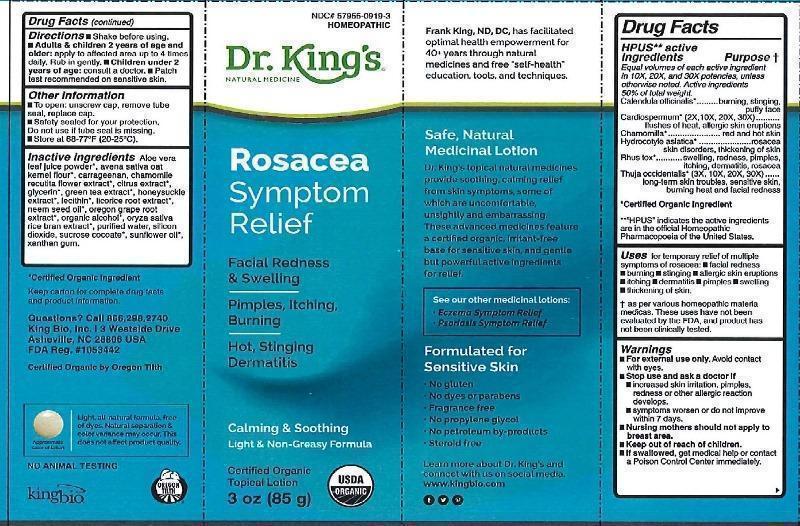 DRUG LABEL: Rosacea Symptom Relief
NDC: 57955-0919 | Form: CREAM
Manufacturer: King Bio Inc.
Category: homeopathic | Type: HUMAN OTC DRUG LABEL
Date: 20170120

ACTIVE INGREDIENTS: CALENDULA OFFICINALIS FLOWERING TOP 10 [hp_X]/83 g; CARDIOSPERMUM HALICACABUM FLOWERING TOP 2 [hp_X]/83 g; MATRICARIA RECUTITA 10 [hp_X]/83 g; CENTELLA ASIATICA 10 [hp_X]/83 g; TOXICODENDRON PUBESCENS LEAF 10 [hp_X]/83 g; THUJA OCCIDENTALIS LEAFY TWIG 3 [hp_X]/83 g
INACTIVE INGREDIENTS: ALOE VERA LEAF; OATMEAL; CARRAGEENAN; CHAMOMILE; CITRUS BIOFLAVONOIDS; GLYCERIN; GREEN TEA LEAF; LONICERA JAPONICA FLOWER; LECITHIN, SOYBEAN; LICORICE; AZADIRACHTA INDICA SEED OIL; MAHONIA AQUIFOLIUM ROOT; ALCOHOL; RICE BRAN; WATER; SILICON DIOXIDE; SUCROSE COCOATE; SUNFLOWER OIL; XANTHAN GUM

Rosacea Symptom Relief

ACTIVE INGREDIENT

Drug Facts__________________________________________________________________________________________________________

HPUS active ingredient Purpose†

Equal volumes of each active ingredient in 10X, 20X, and 30X potencies, unless otherwise noted.

Active ingredients 50% of total weight.

Calendula officinalis, Cardiospermum (2X, 10X, 20X, 30X), Chamomilla, Hydrocotyle asiatica, Rhus tox, Thuja occidentalis (3X, 10X, 20X, 30X).

*"HPUS" indicates the active ingredients are in the official Homeopathic Pharmacopoeia of the United States.

INDICATIONS AND USAGE

Uses for temporary relief of multiple symptoms of rosacea: •facial redness •burning •stinging •allergic skin eruptions •itching •dermatitis •pimples •swelling •thickening of skin.

† as per various homeopathic materia medicas. These uses have not been evaluated by the FDA, and product has not been clinically tested.

Warnings

- For external use only. Avoid contact with eyes.
- Stop use and ask a doctor if •increased skin irritation, pimples, redness or other allergic reaction develops. •symptoms worsen or do not improve within 7 days.
- Nursing mothers should not apply to breast area.
- Keep out of reach of children.
- If swallowed, get medical help or contact a Poison Control Center immediately.

- Keep out of reach of children.

Directions

•Shake before using. •Adults & children 2 years of age and older: apply to affected area up to 4 times daily. Rub in gently. •Children under 2 years of age: consult a doctor. •Patch test recommended on sensitive skin.

Other information:

- To open: unscrew cap, remove tube seal, replace cap.
- Safety sealed for your protection.
- Do not use if tube seal is missing.
- Store at 68-77° (20-25°C).
- Certified organic topical lotion.

INACTIVE INGREDIENT

Inactive ingredients: Aloe vera leaf juice powder*, avena sativa oat kernel flour*, carrageenan, chamomile recutita flower extract*, citrus extract*, glycerin, green tea extract*, honeysuckle extract*, lecithin*, licorice root extract*, neem seed oil*, oregon grape root extract*, organic alcohol*, oryza sativa race bran extract*, silicon dioxide, sucrose cocoate, sunflower oil*, water, xanthan gum.

*Certified Organic Ingredient.

Certified Organic by Oregon Tilth.

PURPOSE

__________________________________________________________________________________________________________

HPUS active ingredient Purpose†

Equal volumes of each active ingredient in 10X, 20X, and 30X potencies, unless otherwise noted.

Active ingredients 50% of total weight.

Calendula officinalis........................................................................burning, stinging, puffy face

Cardiospermum (2X, 10X, 20X, 30X)......................................flush of heat, allergic skin eruptions

Chamomilla....................................................................................................red and hot skin

Hydrocotyle asiatica.....................................................rosacea, skin disorders, thickening of skin

Rhus tox...................................................swelling, redness, pimples, itching, dermatitis, rosacea

Thuja occidentalis (3X, 10X, 20X, 30X).............long-term skin troubles, sensitive skin, burning heat

and facial redness